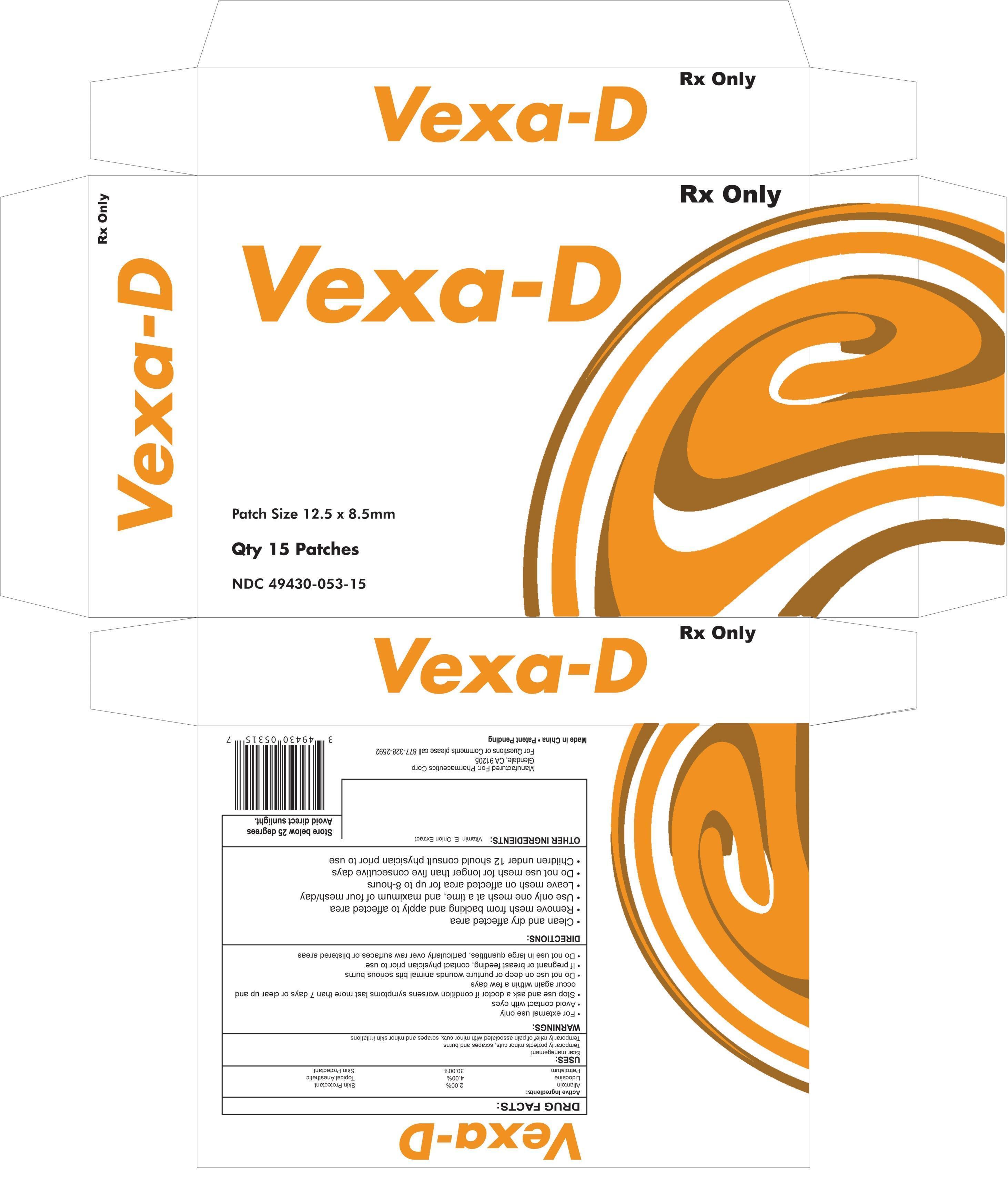 DRUG LABEL: Vexa
NDC: 49430-053 | Form: PATCH
Manufacturer: Pharmaceutics Corporation
Category: prescription | Type: HUMAN PRESCRIPTION DRUG LABEL
Date: 20150324

ACTIVE INGREDIENTS: ALLANTOIN 2 mg/1 1; LIDOCAINE 4 mg/1 1; PETROLATUM 30 mg/1 1
INACTIVE INGREDIENTS: ONION; .ALPHA.-TOCOPHEROL

Vexa-D

Active Ingredients

Allantoin

Lidocaine

Petrolatum

PATIENT INFORMATION

DESCRIPTION:
Vexa-D (Allantoin 2%/Lidocaine 4%/Petrolatum 30%) is comprised of an adhesive material containing Allantoin 2%, Lidocaine 4% and petrolatum 30% which is applied to a woven polyester backing and covered with a PET film release line. The release liner is removed prior to application to the skin. The size of the patch is 12.5 cm x 8.5cm.
Allantoin is chemically designated as 1-(2,5-Dioxo-4-imidazolidinyl). It is a white powder that is stable, incompatible with strong oxidizing agents. It has a melting point of 230°C. It has the following structure:
Lidocaine is chemically designated as 2-(diethylamino)-N-(2,6-dimethylphenyl), has an octanol: water partition ration of 43 at pH 7.4, and has the following structure:
Each adhesive patch contains 34 mg of Allantoin and 68 mg of Lidocaine in a petrolatum base. It also contains the following inactive ingredients: Vitamin E and Onion Extract.
CLINICAL PHARMACOLOGY:
Pharmacodynamics
Allantoin works by slowing bacterial growth and loosing and softening scales and crust. The keratolytic effect and abrasive and astringent properties of Allantoin are used in skin softening cosmetic preparation.
Allantoin is a moisturizing, soothing, healing, anti-irritating, keratoyltic and non-toxic agent. Allantoin is a cell-proliferation healing agent which stimulates healthy tissue formation. It removes necrotic and scaling tissue.
Lidocaine is an amide-type local anesthetic agent and is suggested to stabilize neuronal membranes by inhibiting the ionic fluxes required for the initiation and conduction of impulses.
The penetration of Lidocaine into intact skin after application of patch is sufficient to produce an analgesic effect, but less than the amount necessary to produce a complete sensory block.
Pharmacokinetics
Absorption
The amount of allantoin and lidocaine systemically absorbed is directly related to both the duration of application and the surface area over which it is applied.
In a pharmacokinetic study, three lidocaine 5% patches were applied over an area of 420 cm2 of intact skin on the back of normal volunteers for 12 hours. Blood samples were withdrawn for a determination of lidocaine concentration during the application and for 12 hours after removal of patches. The results are summarized in table 1.
Table 1
Absorption of Lidocaine
Normal volunteers (n=15, 12-hour wearing time)
Application Site
Area
(cm2)
Dose Absorbed (mg)
Cmax
(μg/mL)
Tmax
(hr)
3 Patches (2100 mg)
Back
420
64 ± 32
0.13 ± 0.06
11 hr
When lidocaine 5% patch is used according to the recommended dosing instructions, only 3 ± 2% of the dose applied is expected to be absorbed. At least 95% (665 mg) of lidocaine will remain in a used patch. Mean peak blood concentration of lidocaine is about 0.13 μg/mL (about 1/10 of the therapeutic concentration required to treat cardiac arrhythmias). Repeated application of three days, indicated that the lidocaine concentration does not increase with daily use.
Study of allantoin 1% solution absorption in oil/water cream applied to the inner forearm of volunteers (n=6) to test skin penetration was performed. Two applications were made, 1 removed after 3 hours and the other after 6 hours. The remaining allantoin in the removed portion was measured and subtracted from the original amount to determine the absorption. Allantoin penetration with the oil/water cream was 13.0% ± 1.8% and 15.4% ± 2.7%
Metabolism
It is not known if lidocaine is metabolized in the skin. Lidocaine is metabolized rapidly by the liver to a number of metabolites, including menoethylglycinexylidie (MEGX) and glycinexylidide (GX), both of which have pharmacologic activity similar to, but less potent than that of lidocaine. A minor metabolite, 2,6-xylidine, has unknown pharmacologic activity but is carcinogenic in rats. The blood concentration of this metabolite is negligible following application of lidocaine 5% patch. Following intravenous administration, MEGX and GX concentrations in serum range from 11 to 36% and from 5 to 11% of lidocaine concentrations, respectively.
Allantoin is not metabolized in the human body and is excreted in urine.
Excretion
Lidocaine and its metabolites are excreted by the kidneys. Less than 10% of lidocaine is excreted unchanged. The half-life of lidocaine elimination from plasma following IV administration is 81 to 149 minutes (mean 107 ± 22 SD, n=15). The systemic clearance is 0.33 to 0.90 L/min (mean 0.64 ± 0.18 SD, n=15).
Allantoin is excreted by the kidneys. Majority of Allantoin is excreted unchanged.
INDICATIONS AND USAGE
Vexa-D is indicated for scar management. It is indicated for the temporary relief of pain associated with minor cuts, scrapes and minor skin irritations. Protects minor cuts, scrapes and burns.
CONTRAINDICATIONS
Vexa-D is contraindicated in patients with a known history of sensitivity to local anesthetics of the amide type, or to any other component of the product.
WARNINGS
Accidental Exposure in Children
Even a used Vexa-D patch contains a large amount of lidocaine. The potential exists for a small child or a pet to suffer serious adverse effects from chewing or ingesting a new or used Vexa-D patch, although the risk with this formulation has not been evaluated. It is important for patients to store and dispose of Vexa-D out of the reach of children, pets and others. (See HANDLING AND DISPOSAL)
Excessive Dosing
Excessive dosing by applying Vexa-D to larger areas for longer than the recommended wearing time could result in increased absorption of lidocaine and high blood concentrations, leading to serious adverse effects. Lidocaine toxicity could be expected at lidocaine blood concentrations above 5 μg/mL. The blood concentration of lidocaine is determined by the rate of systemic absorption and elimination. Longer duration of application, application of more than the recommended number of patches, smaller patients, or impaired elimination may all contribute to increasing the blood concentration
of lidocaine. With recommended dosing of Vexa-D, the average blood concentration is about 0.13 μg/mL, but concentration higher than 0.25 μg/mL have been observed in some patients.
PRECAUTIONS
General
Hepatic Disease
Patients with severe hepatic disease are at greater risk of developing toxic blood concentrations of lidocaine, because of their inability to metabolize lidocaine normally.
Allergic Reactions
Patients allergic to para-aminobenzoic acid derivatives (procaine, tetracaine, benzocaine, etc.) have not shown cross sensitivity to lidocaine. However, Vexa-D should be used with caution in patients with a history of drug sensitivities, especially if the etiologic agent is uncertain.
Non-intact Skin
Application to broken or inflamed skin, although not tested, may result in higher blood concentrations of lidocaine from increased absorption. Vexa-D is only recommended for use on intact skin.
Eye Exposure
The contact of Vexa-D with eyes, although not studied, should be avoided based on the findings of severe eye irritations with the use of similar products in animals. If eye contact occurs, immediately wash out the eye with water or saline and protect the eye until sensation returns.
Drug Interactions
Antiarrhythmic Drugs
Vexa-D should be used with caution in patients receiving Class 1 antiarrhythmic drugs (such as tocainide and mexiletine) since the toxic effects are additive and potentially synergistic.
Local Anesthetics
When Vexa-D is used concomitantly with other products containing local anesthetic agents the amount absorbed from all formulations must be considered.
Pregnancy
Teratogenic Effects
Pregnancy Category B
Vexa-D (Allantoin 2%/Lidocaine 4%/petrolatum30% patch) has not been studied in pregnancy. Reproduction studies with lidocaine have been performed in rats at doses up to 30 mg/kg subcutaneously and have revealed no evidence if harm to the fetus due to lidocaine. There are, however, no adequate and well-controlled studies in pregnant women. Because animal reproduction studies are not always predictive of human response, Vexa-D should be used during pregnancy only if clearly needed.
Nursing Mothers
Vexa-D has not been studied in nursing mothers. Lidocaine is excreted in human milk, and the milk: plasma ration of lidocaine is 0.4. Caution should be exercised when Vexa-D is administered to a nursing mother.
Pediatric Use
Safety and effectiveness in pediatric patients have not been established.
ADVERSE REACTIONS
Application Site Reactions
During or immediately after treatment with Vexa-D (Allantoin 2%/Lidocaine 4%/petrolatum30% patch), the skin at the site of application may develop blisters, bruising, burning sensation, depigmentation, dermatitis, discoloration, edema, erythema, exfoliation, irritation, papules, petechia, pruritus, vesicles or may be the locus of abnormal sensation. These reactions are generally mild and transient, resolving spontaneously within a few minutes to hours.
Allergic Reactions
Allergic and anaphylactoid reactions associated with lidocaine, although rare, can occur. They are characterized by angioedema, bronchospasm, dermatits, dyspnea, hypersensitivity, laryngospasm, pruritus, shock, and urticaria. If they occur, they should be managed by conventional means, the detection of sensitivity by skin testing is of doubtful value.
OVERDOSAGE
Lidocaine overdose from cutaneous absorption is rare, but could occur. If there is any suspicion of lidocaine overdose, drug blood concentration should be checked. The management of overdose includes close monitoring, supportive care, and symptomatic treatment. Dialysis is of negligible value in the treatment of acute overdose with lidocaine.
In the absence of massive topical overdose or oral ingestion, evaluation of symptoms of toxicity should include consideration of other etiologies for the clinical effects, or over dosage from other sources of lidocaine or other local anesthetics.
The oral LD50 of lidocaine HCl is 459 (346-773) mg/kg (as the salt) in non-fasted female rats and 214 (154-324) mg/kg (as the salt) in fasted female rats, which are equivalent to roughly 4000 mg and 2000 mg, respectively in a 60 to 70 kg man based on the equivalent surface area dosage conversion factors between species.
DOSAGE AND ADMINISTRATION
Apply Vexa-D to intact skin to cover the most painful area. Apply up to four patches per day. Each patch should not be applied for more than 8 hours in a given 24-hour period. Patches may be cut into smaller sizes with scissors prior to removal of the release liner. Clothing may be worn over the area of application. Smaller areas of treatment are recommended in a debilitated patient, or a patient with impaired elimination.
If irritation or a burning sensation occurs during application, remove the patch and do not reapply until the irritation subsides.
When Vexa-D is used concomitantly with other products containing local anesthetic agents, the amount absorbed from all formulations must be considered.
HANDLING AND DISPOSAL
Hands should be washed after handling of Vexa-D, and eye contact with Vexa-D should be avoided. Do not store patch outside the sealed envelope. Apply immediately after removal from the protective envelope. Fold use patches so that the adhesive side sticks to itself and safely discard used patches or pieces of cut patches where children and pets cannot get to them. Vexa-D should be kept out of reach of children.
HOW SUPPLIED
Vexa-D (Allantoin 2%/Lidocaine 4%/petrolatum30% patch) is available as the following:
Box of 15 patches, packaged into 3 child-resistant envelopes (5 patches/envelope)
NDC 45861-008-15
Store below 25°C (77° F); excursion permitted to 15°-30°C (59°-86° F). [See USP Controlled Room Temperature].
Manufactured for:
Pharmaceutics Corporation
Glendale, CA 91205
February 2015

Other Ingredients

Vitamin E, Onion Extract

PURPOSE

Skin Protectant

Topical Anesthetic

Skin Protectant

Warnings

For external use only

Avoid contact with eyes

Stop use and ask a doctor if condition worsens, symptoms last more than 7 dasy or clear up and occure again within a few days

Do not use on deep puncture wounds, animal bites, serious burns

If pregnant or breast feeding, contact physician prior to use

Do not use in large quantities, particularly over raw sufaces or blistered areas

Uses

Scar management

Temporarily protects minor cuts, scrapes and burns

Temporarily relief of pain associated with minor cuts, scrapes and minor skin irritations

Directions

Clean and dry affected area

Remove mesh from backing and apply to affected area

Use only one mesh at a time, and maximum of four mesh/day

Leave mesh on affected area for up to 8 hours

Do not use mesh for longer than five consecutive days

Children under 12 should consult physician prior to use

STORAGE AND HANDLING

Store below 25 degrees. Avoid direct sunlight.